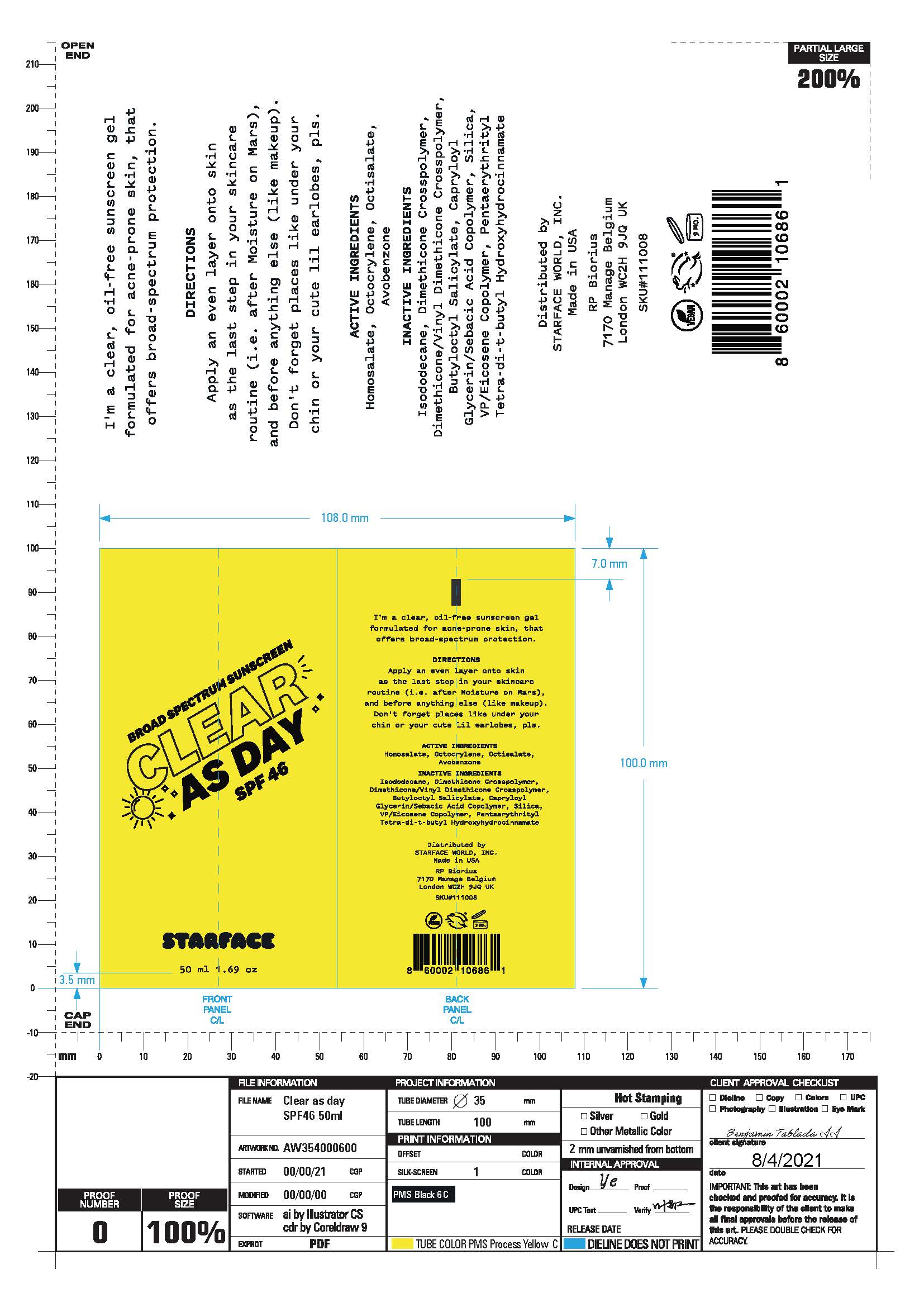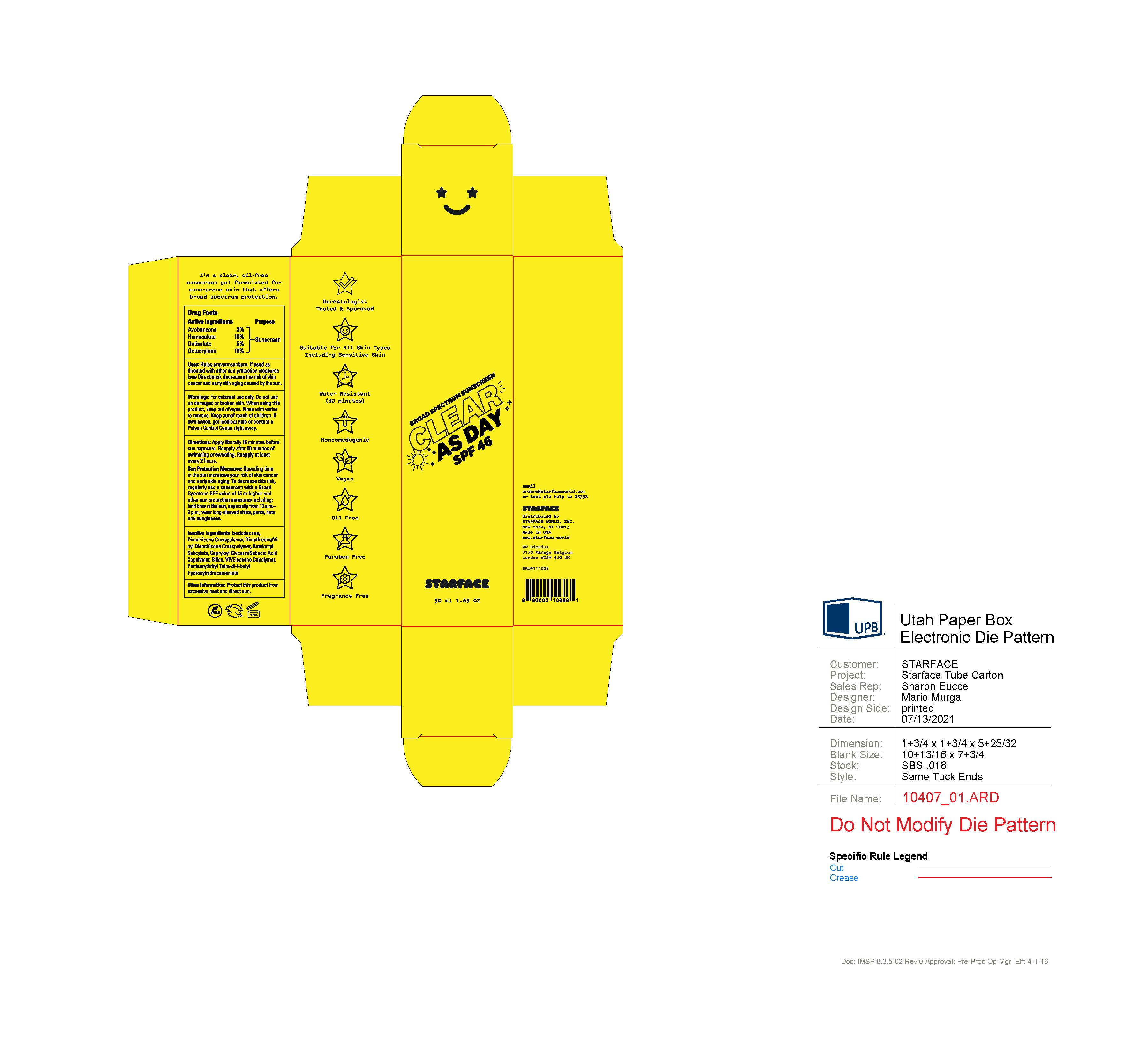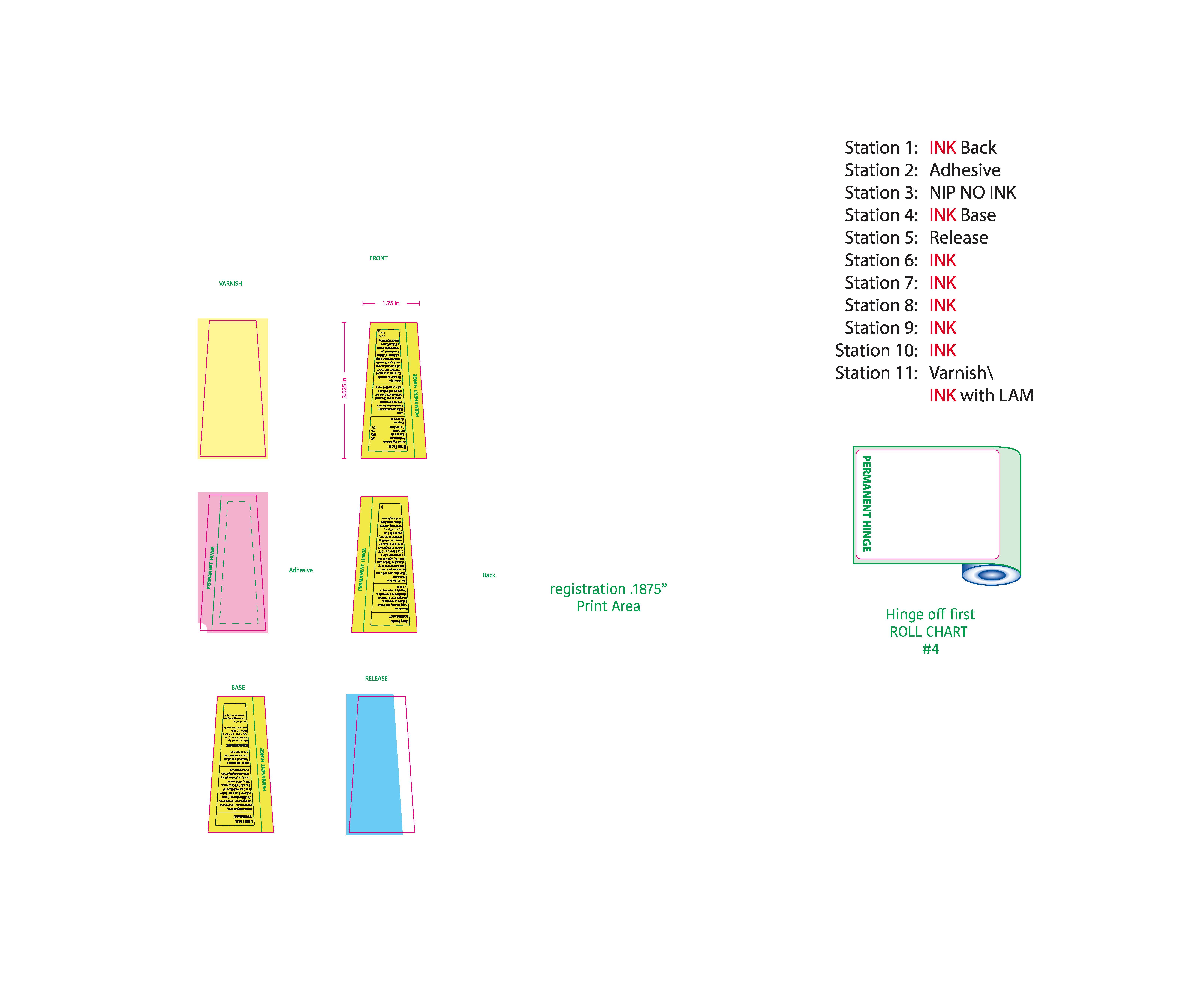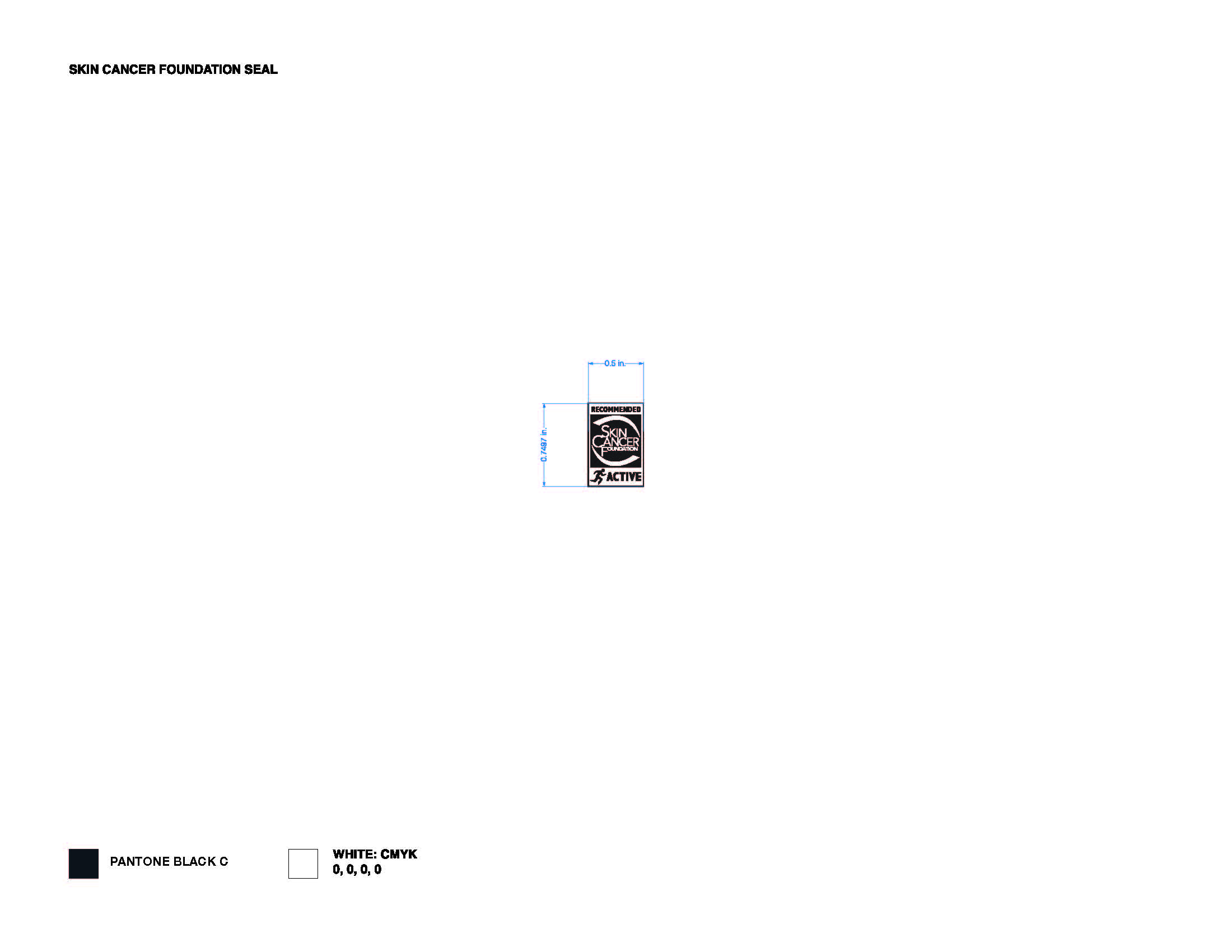 DRUG LABEL: Sunscreen
NDC: 61354-047 | Form: GEL
Manufacturer: Oxygen Development, LLC
Category: otc | Type: HUMAN OTC DRUG LABEL
Date: 20230203

ACTIVE INGREDIENTS: OCTISALATE 5 mg/100 mg; HOMOSALATE 10 mg/100 mg; AVOBENZONE 3 mg/100 mg; OCTOCRYLENE 10 mg/100 mg
INACTIVE INGREDIENTS: ISODODECANE 49.8 mg/100 mg; CAPRYLOYL GLYCERIN/SEBACIC ACID COPOLYMER (2000 MPA.S) 2 mg/100 mg; DIMETHICONE/VINYL DIMETHICONE CROSSPOLYMER (SOFT PARTICLE) 2.85 mg/100 mg; VINYLPYRROLIDONE/EICOSENE COPOLYMER 1.25 mg/100 mg; BUTYLOCTYL SALICYLATE 2 mg/100 mg; DIMETHICONE CROSSPOLYMER (450000 MPA.S AT 12% IN CYCLOPENTASILOXANE) 12.46 mg/100 mg; ALUMINUM HEXAFLUOROSILICATE NONAHYDRATE 1.5 mg/100 mg

Broad Spectrum Sunscreen Clear as Day SPF 46 Starface

Active ingredient

Avobenzone 3%

Homosalate 10%

Octisalate 5%

Octocrylene 10%

Uses

Helps prevent sunburn. If used as directed with another sun protection measures (see Directions), decreasses the risk of skin cancer and early skin aging caused by the sun.

Warnings

For external use only. Do not use on damage or broken skin. When using this product, keep out of eyes. Rinse with water to remove. Keep out of reach of children. If swallowed, get medical help or contact a Poison Control Center rigth away

Directions

Apply liberally 15 minutes before sun exposure. Reapply after 80 minutes of swimming or sweating. Reapply at least every 2 hours.

Sun protection meassures: Spending time in the sun increasses your risk of skin cancer and early skin aging. To decrease this risk, regularly use a sunscreen with a broad Spectrum SPF value of 15 or higher and other sun protection measures including: limit time in the sun, specially from 10 am - 2 pm, wear long-sleeved shirts, pants, hats and sunglasses.

Inactive ingredients

Isododecane, Dimethicone Crosspolymer, Dimethicone/Vinyl Dimethicone Crosspolymer, Butyloctyl Salicylate, Capryloyl Glycerin/Sebacic Acid Copolymer, Silica, VP/Eicosene Copolymer, Pentaerythrityl Tetra-di-t-butyl Hydroxyhydrocinnamate